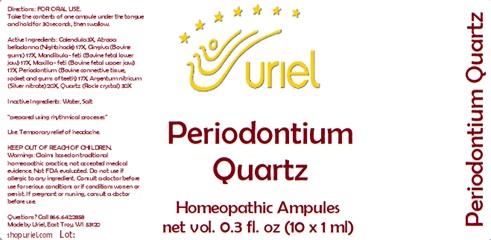 DRUG LABEL: Periodontium Quartz
NDC: 48951-8017 | Form: LIQUID
Manufacturer: Uriel Pharmacy Inc.
Category: homeopathic | Type: HUMAN OTC DRUG LABEL
Date: 20240426

ACTIVE INGREDIENTS: CALENDULA OFFICINALIS FLOWERING TOP 3 [hp_X]/1 mL; ATROPA BELLADONNA 17 [hp_X]/1 mL; BEEF TONGUE 17 [hp_X]/1 mL; BOS TAURUS BONE 17 [hp_X]/1 mL; SUS SCROFA TOOTH 17 [hp_X]/1 mL; SILVER 20 [hp_X]/1 mL; SILICON DIOXIDE 30 [hp_X]/1 mL
INACTIVE INGREDIENTS: SODIUM CHLORIDE; WATER

Periodontium Quartz

INDICATIONS AND USAGE

Directions: FOR ORAL USE.

DOSAGE AND ADMINISTRATION

Take the contents of one ampule under the tongue and hold for 30 seconds, then swallow.

ACTIVE INGREDIENT

Active Ingredients: Calendula ex herba 3X, Atropa belladonna ex herba 17X, Gingiva 17X, Mandibula (feti) 17X, Maxilla (feti) 17X, Periodontium 17X, Argentum nitricum 20X, Quartz 30X

Inactive Ingredients: Water, Salt

"prepared using rhythmical processes"

PURPOSE

Use: Temporary relief of headache.

KEEP OUT OF REACH OF CHILDREN.

WARNINGS

Warnings: Claims based on traditional homeopathic practice, not accepted medical evidence. Not FDA evaluated. Do not use if allergic to any ingredient. Consult a doctor before use for serious conditions or if conditions worsen or persist. If pregnant or nursing, consult a doctor before use.

QUESTIONS

Questions? Call 866.642.2858 Made by Uriel, East Troy, WI 53120 shopuriel.com Lot: